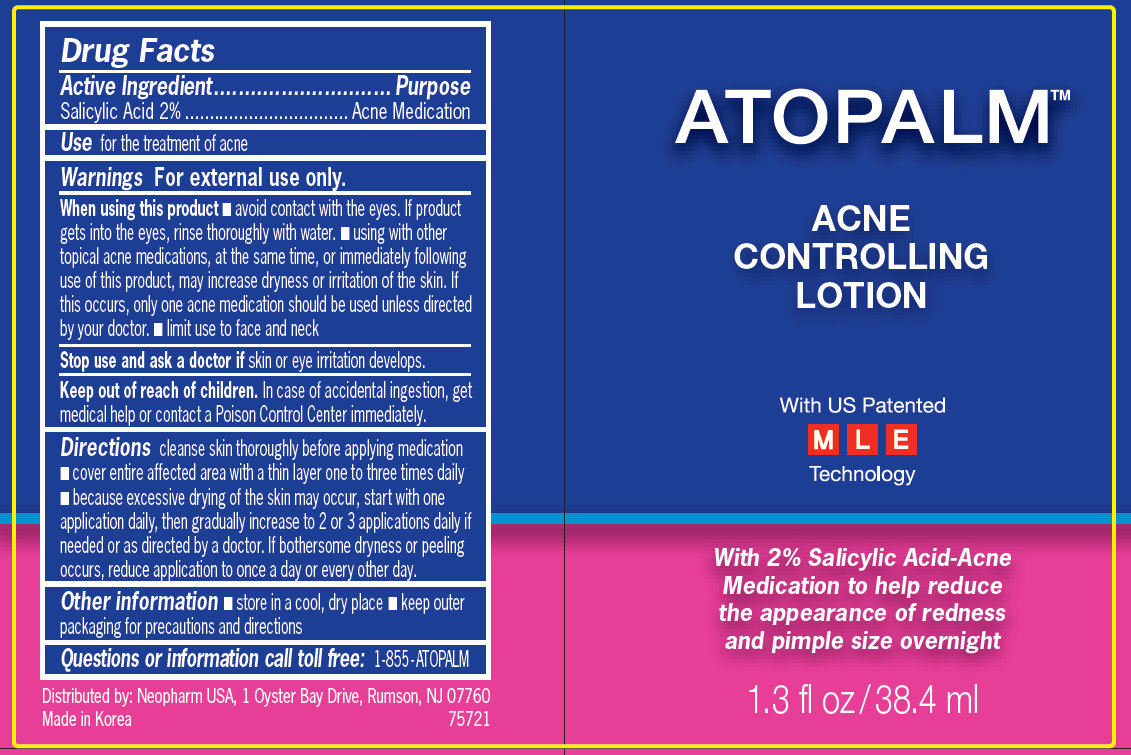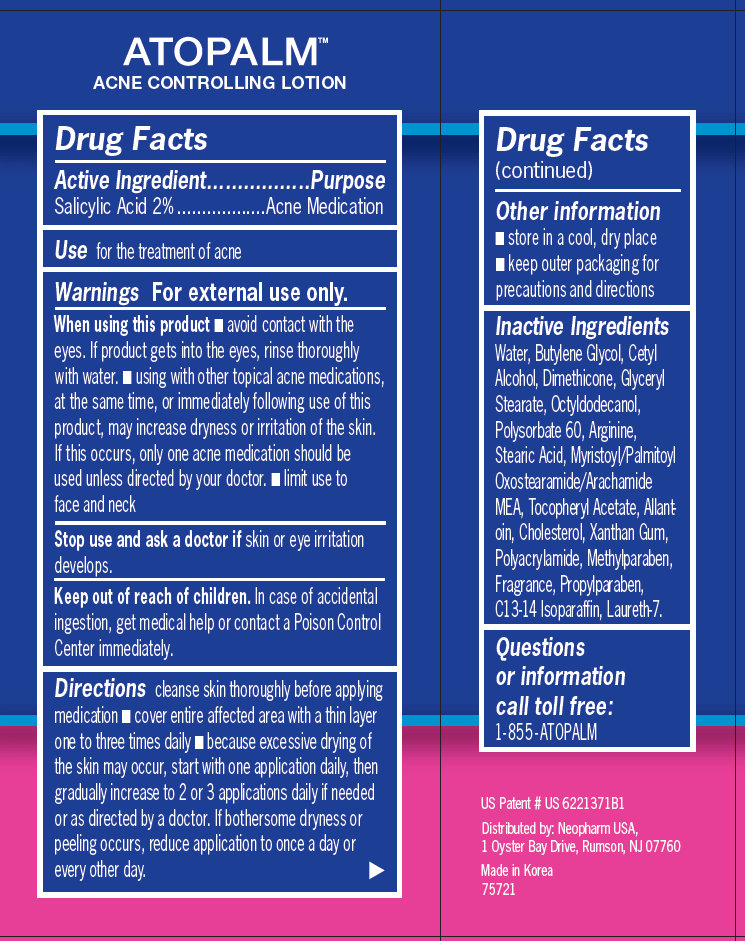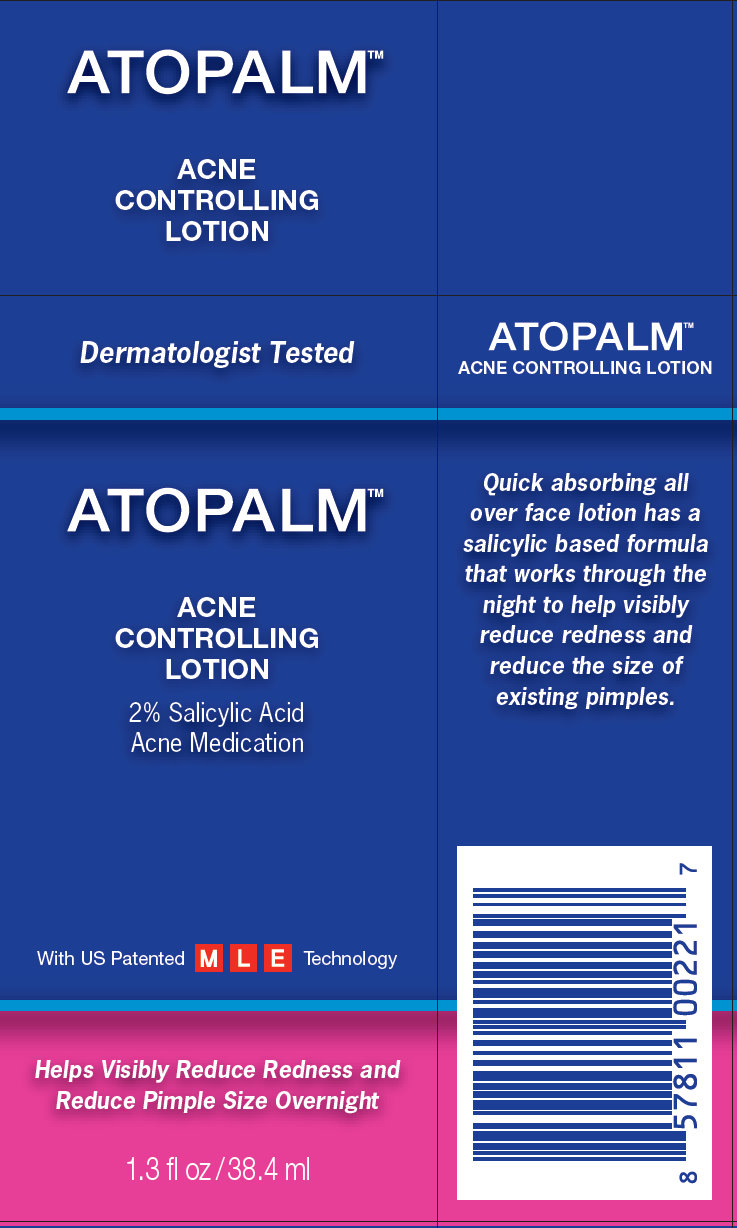 DRUG LABEL: Atopalm Acne Controlling
                        
NDC: 51141-7000 | Form: LOTION
Manufacturer: NeoPharm Co., Ltd.
Category: otc | Type: HUMAN OTC DRUG LABEL
Date: 20111109

ACTIVE INGREDIENTS: SALICYLIC ACID 2 mL/100 mL
INACTIVE INGREDIENTS: WATER; BUTYLENE GLYCOL; CETYL ALCOHOL; DIMETHICONE; GLYCERYL MONOSTEARATE; OCTYLDODECANOL; POLYSORBATE 60; ARGININE; STEARIC ACID; MYRISTOYL/PALMITOYL OXOSTEARAMIDE/ARACHAMIDE MEA; ALLANTOIN; CHOLESTEROL; XANTHAN GUM; POLYQUATERNIUM-7 (70/30 ACRYLAMIDE/DADMAC; 1600 KD); METHYLPARABEN; PROPYLPARABEN; C13-14 ISOPARAFFIN; LAURETH-7

Atopalm Acne Controlling Lotion

Active Ingredient

Active Ingredient..................................Purpose
Salicylic Acid 2% ..................Acne Medication

Use

for the treatment of acne

Warnings

For external use only.

When using this product

- avoid contact with the eyes. If product gets into the eyes, rinse thoroughly with water. - using with other topical acne medications, at the same time, or immediately following use of this product, may increase dryness or irritation of the skin. If this occurs, only one acne medication should be used unless directed by your doctor. - limit use to face and neck

Stop use and ask a doctor

if skin or eye irritation develops.

Keep out of reach of children

Ask Doctor

In case of accidental ingestion, get medical help or contact a Poison Control Center immediately.

Directions

cleanse skin thoroughly before applying medication - cover entire affected area with a thin layer one to three times daily - because excessive drying of the skin may occur, start with one application daily, then gradually increase to 2 or 3 applications daily if needed or as directed by a doctor. If bothersome dryness or peeling occurs, reduce application to once a day or every other day.

Other information

- store in a cool, dry place - keep outer packaging for precautions and directions

Inactive Ingredients

Water, Butylene Glycol, Cetyl Alcohol, Dimethicone, Glyceryl Stearate, Octyldodecanol, Polysorbate 60, Arginine, Stearic Acid, Myristoyl/Palmitoyl Oxostearamide/Arachamide MEA, Tocopheryl Acetate, Allantoin, Cholesterol, Xanthan Gum, Polyacrylamide, Methylparaben, Fragrance, Propylparaben, C13-14 Isoparaffin, Laureth-7.

Questions or information call toll free: 1-855 - ATOPALM

Purpose

Acne Medication

Description

US Patent # US 6221371B1 Distributed by: Neopharm USA, 1 Oyster Bay Drive, Rumson, NJ 07760 Made in Korea 75721 Quick absorbing all over face lotion has a salicylic based formula that works through the night to help visibly reduce redness and reduce the size of existing pimples.

PACKAGE LABEL

ATOPALM ACNE CONTROLLING LOTION With US Patented MLE Technology With 2% Salicylic Acid-Acne Medication to help reduce the appearance of redness and pimple size overnight 1.3 fl oz /38.4 ml Drug Facts
Active Ingredient............................. ....................Purpose
Salicylic Acid 2% ................................. Acne Medication
Use for the treatment of acne Warnings For external use only. When using this product - avoid contact with the eyes. If product gets into the eyes, rinse thoroughly with water. - using with other topical acne medications, at the same time, or immediately following use of this product, may increase dryness or irritation of the skin. If this occurs, only one acne medication should be used unless directed by your doctor. - limit use to face and neck Stop use and ask a doctor if skin or eye irritation develops. Keep out of reach of children. In case of accidental ingestion, get medical help or contact a Poison Control Center immediately. Directions cleanse skin thoroughly before applying medication - cover entire affected area with a thin layer one to three times daily - because excessive drying of the skin may occur, start with one application daily, then gradually increase to 2 or 3 applications daily if needed or as directed by a doctor. If bothersome dryness or peeling occurs, reduce application to once a day or every other day. Other information - store in a cool, dry place - keep outer packaging for precautions and directions Questions or information call toll free: 1-855-ATOPALM Distributed by: Neopharm USA, 1 Oyster Bay Drive, Rumson, NJ 07760 Made in Korea 75721

PACKAGE LABEL

ATOPALM ACNE CONTROLLING LOTION US Patent # US 6221371B1 Distributed by: Neopharm USA, 1 Oyster Bay Drive, Rumson, NJ 07760 Made in Korea 75721

PACKAGE LABEL

ATOPALM ACNE CONTROLLING LOTION Dermatologist Tested ATOPALM ACNE CONTROLLING LOTION ATOPALM ACNE CONTROLLING LOTION 2% Salicylic Acid Acne Medication Quick absorbing all over face lotion has a salicylic based formula that works through the night to help visibly reduce redness and reduce the size of existing pimples. With US Patented M L E Technology Helps Visibly Reduce Redness and Reduce Pimple Size Overnight 1.3 fl oz /38.4 ml 8 57811 00221 7